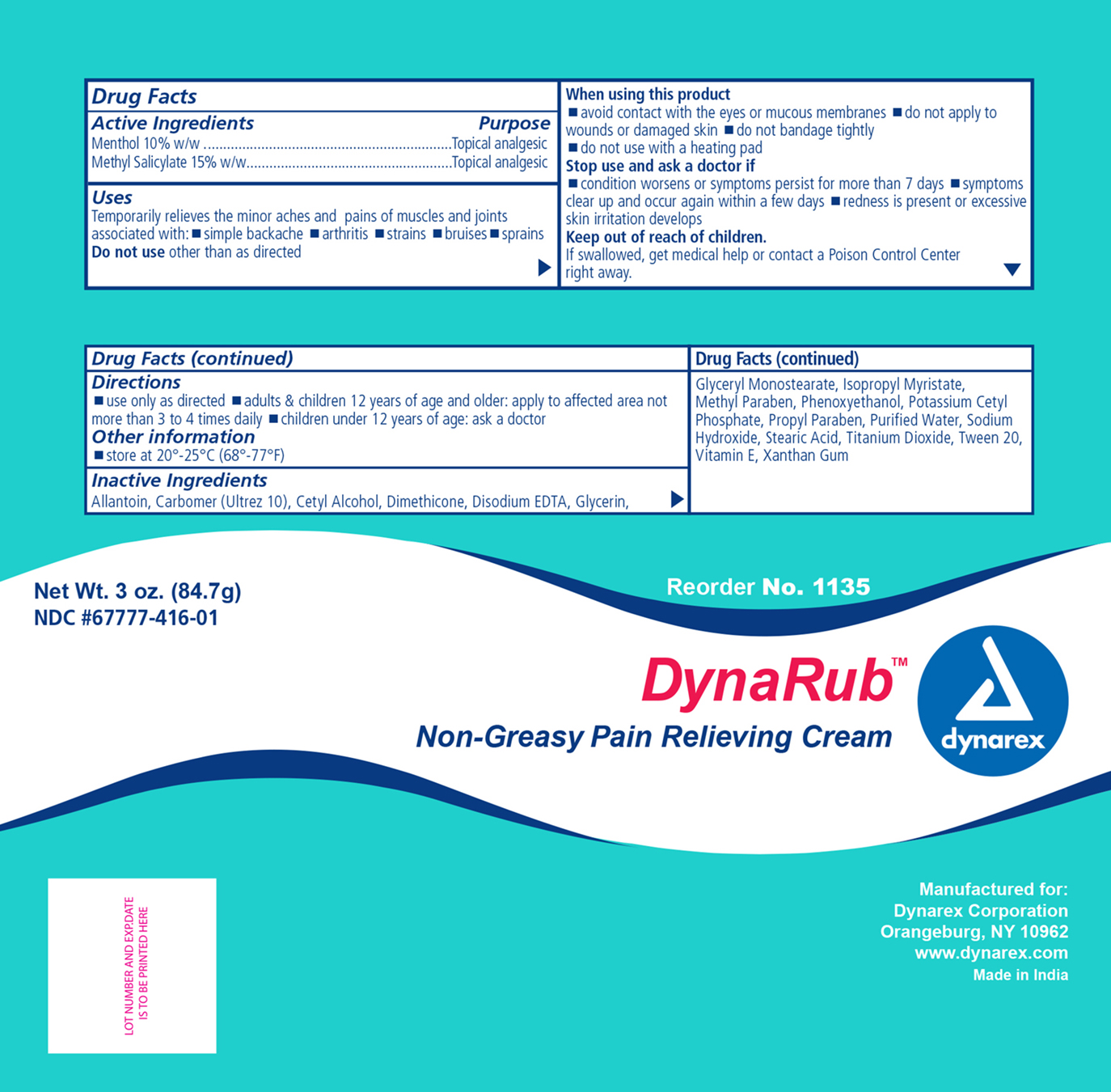 DRUG LABEL: Dynarex Muscle Rub Cream
NDC: 67777-416 | Form: CREAM
Manufacturer: Dynarex Corporation
Category: otc | Type: HUMAN OTC DRUG LABEL
Date: 20170615

ACTIVE INGREDIENTS: MENTHOL 10 mg/1 g; METHYL SALICYLATE 15 mg/1 g
INACTIVE INGREDIENTS: CETYL ALCOHOL; EDETATE DISODIUM; POTASSIUM CETYL PHOSPHATE; XANTHAN GUM; GLYCERIN; CARBOMER 940; ALLANTOIN; METHYLPARABEN; PROPYLPARABEN; POLYSORBATE 20; GLYCERYL MONOSTEARATE; ISOPROPYL MYRISTATE; STEARIC ACID; SODIUM HYDROXIDE; TITANIUM DIOXIDE; DIMETHICONE; PHENOXYETHANOL; ALPHA-TOCOPHEROL; WATER

Dynarex Muscle Rub Cream

Active Ingredient

Active Ingredient Purpose

Menthol 10% Topical analgesic

Methyl salicylate 15% w/w Topical analgesic

Purpose

Temporary relief of minor aches and pains of muscle joints associated with:

- simple backache
- arthritis
- strains
- bruises
- sprains

Do not use other than directed.

Indications and Usage

Uses

Temporary relief of minor aches and pains of sore muscles and joints.

Warnings

For external use only.

- Avoid contact with the eyes or mucous membranes.
- Do not apply to wounds or damaged skin.
- Do not bandage tightly.
- Do not use with heating pad or device.

Stop Use

Stop Use And Ask A Doctor If:

- Condition worsens, or if symptoms persist for more than 7 days,
- symptoms clear up and occur again in a few days
- redness is present or excessive skin irritation develops

Keep Out Of Reach Of Children

If accidentally ingested, get medical help or contact a Poison Control Center immediately.

Dosage & Administration

Directions

- Use only as directed
- Adults and children 12 years of age and older: apply to the affected areas not more than 3 or 4 times daily.
- Children under 12 years of age: Consult a physician.

Other Information

Store at 20° - 25°C (68°-77°F)

Inactive Ingredients

Allantoin, carbomer, cetyl alcohol, dimethicone, disodium EDTA, glycerin, glyceral monostearate, isopropyl myristate, methyparaben, phenoxyethanol, potassium cetyl phoshate, propylparaben, purified water, sodium hydroxide, stearic acid, titanium dioxide, polysorbate 20, Vitamin E, xanthan gum.

Principal Display panel

1135 GV.jpg